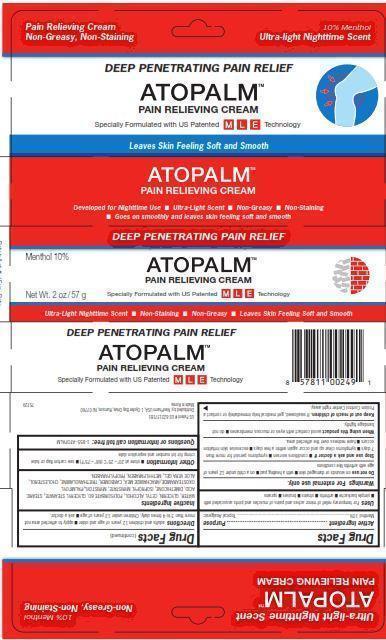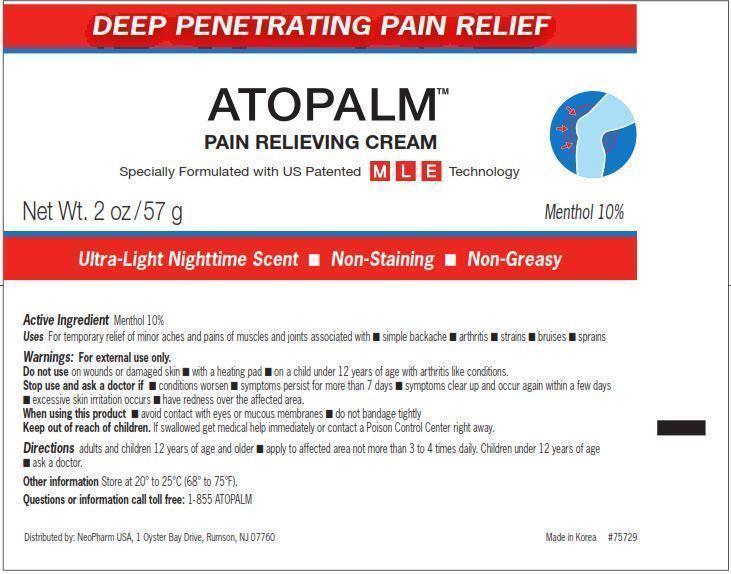 DRUG LABEL: ATOPALM PAIN RELIEVING
NDC: 51141-0239 | Form: CREAM
Manufacturer: NeoPharm Co., Ltd.
Category: otc | Type: HUMAN OTC DRUG LABEL
Date: 20120815

ACTIVE INGREDIENTS: MENTHOL 10 g/100 g
INACTIVE INGREDIENTS: WATER; GLYCERIN; CETYL ALCOHOL; POLYSORBATE 60; GLYCERYL MONOSTEARATE; STEARIC ACID; DIMETHICONE; ISOPROPYL MYRISTATE; MYRISTOYL/PALMITOYL OXOSTEARAMIDE/ARACHAMIDE MEA; TROLAMINE; CHOLESTEROL; ALOE VERA LEAF; METHYLPARABEN; PROPYLPARABEN

ATOPALM PAIN RELIEVING CREAM

Drug Facts

Active ingredient

Menthol 10%

Purpose

Topical Analgesic

INDICATIONS AND USAGE

Uses For temporary relief of minor aches and pains of muscles and joints associated with

- simple backache
- arthritis
- strains
- bruises
- sprains

Warnings For external use only.

Do not use

- on wounds or damaged skin
- with a heating pad
- on a child under 12 years of age with arthritis like conditions

Stop use and ask a doctor if

- conditions worsen
- symptoms persist for more than 7 days
- symptoms clear up and occur again within a few days
- excessive skin irritation occurs
- have redness over the affected area.

When using this product avoid contact with eyes or mucous membranes, do not bandage tightly.

Keep out of reach of children. If swallowed, get medical help immediately or contact a Poison Control Center right away.

Directions
adults and children 12 years of age and older
apply to affected area not more than 3 to 4 times daily
Children under 12 years of age
ask a doctor

Inactive Ingredients

WATER, GLYCERIN, CETYL ALCOHOL, POLYSORBATE 60, GLYCERYL STEARATE, STEARIC ACID, DIMETHICONE, ISOPROPYL MYRISTATE, MYRISTOYL/PALMITOYL OXOSTEARAMIDE/ARACHAMIDE MEA, CARBOMER, TRIETHANOLAMINE, CHOLESTEROL, ALOE VERA GEL, METHYLPARABEN, PROPYLPARABEN.

Other Information

store at 20 - 25 degrees Celsius (68 - 75 degrees Fahrenheit)

see carton or flap or tube crimp for lot number and expiration date

QUESTIONS

Questions or information call toll free: 1-855-ATOPALM

US Patent # US 6221371B1

Distributed by: NeoPharm USA, 1 Oyster Bay Drive, Rumson, NJ 07760

Made in Korea

PACKAGE LABEL

Pain Relieving Cream
Non-Greasy, Non-Staining

10% Menthol
Ultra-light Nighttime Scent

DEEP PENETRATING PAIN RELIEF

ATOPALM (TM)

Developed for Nighttime Use

Goes on smoothly and leaves skin feeling soft and smooth

Net. Wt. 2 oz/57 g

Specially Formulated with US Patented MLE Technology